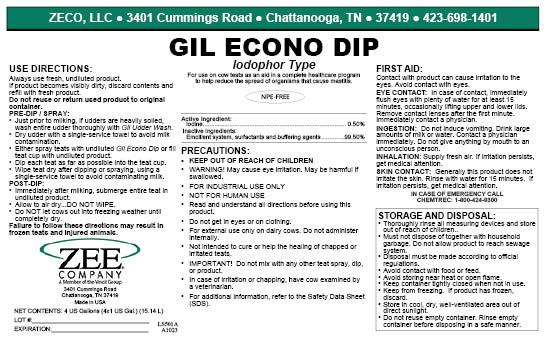 DRUG LABEL: Gil Econo Dip
NDC: 86161-005 | Form: LIQUID
Manufacturer: ZECO, LLC
Category: animal | Type: OTC ANIMAL DRUG LABEL
Date: 20240123

ACTIVE INGREDIENTS: IODINE 5000 mg/1 L
INACTIVE INGREDIENTS: C12-16 PARETH-5; ANHYDROUS CITRIC ACID; SODIUM HYDROXIDE; GLYCERIN

Gil Econo Dip

USER SAFETY WARNINGS

Idophor-Type Teat Dip for Dairy Cows

For External Use Only on Dairy Cows

WARNING! May Cause Eye Irritation.
May Be Harmful If Swallowed.

Keep Out Of Reach Of Children

Use on each teat as an aid in a complete cow health care program to help reduce the spread of organisms that may cause mastitis.

Not intended to cure or help the healing of chapped or irritated teats.

In case of irritation or chapping, have cow examined by a veterinarian.

Active Ingredient

Iodine ................................................................................ 0.50%

Inactive Ingredients

Emollient system, surfactants and buffering agents.............. 99.50%

FIRST AID

EYES: Immediately flush eyes with plenty of water for at least 15 minutes occasionally lifting the upper and lower lids. Contact a physician immediately.

INGESTION: Do NOT induce vomiting. Drink large amounts of milk or water. Contact a physician immediately. Do not give anything by mouth to an unconscious person.

Precautions

- KEEP FROM FREEZING. If frozen, discard.
- Do NOT get in eyes or on clothing.
- Do NOT take internally.
- Do NOT allow to contaminate food.
- Wash thoroughly after handling.
- Keep container tightly closed when not in use.
- Store in a cool, dry, well-ventilated area out of direct sunlight.

DOSAGE AND ADMINISTRATION

Important

Do NOT mix with any other teat spray, dip, or product.

Use Directions

Always use fresh, undiluted product. If product becomes visibly dirty, discard contents and refill with fresh product. Do NOT reuse or return used product to original container.

- PRE-DIP/SPRAY: Just prior to milking, if udders are heavily soiled, wash entire udder thoroughly with Gil Udder Wash. Dry udder with a single-service towel to avoid milk contamination.
  Either spray teats with undiluted Gil Ultra Dip or fill teat cup with undiluted product. Dip each teat as far as possible into the teat cup. Wipe teat dry after dipping or spraying using a single-service towel to avoid contaminating milk.
- POST-DIP: Immediately after milking, submerge entire teat in undiluted product. Allow to air dry—do NOT wipe. Do NOT let cows out in freezing weather until completely dry.

PACKAGE LABEL

Add image transcription here...